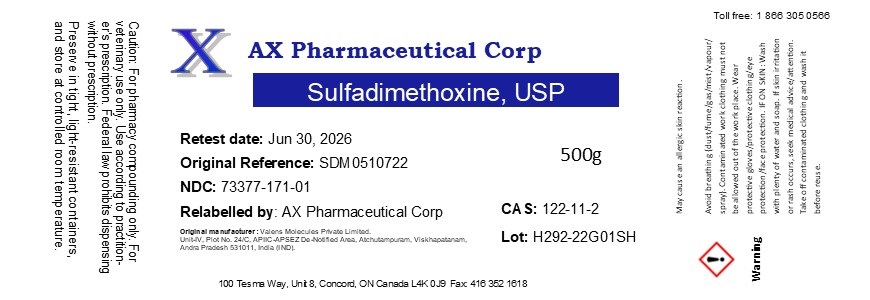 DRUG LABEL: Sulfadimethoxine
NDC: 73377-171 | Form: POWDER
Manufacturer: AX Pharmaceutical Corp
Category: other | Type: BULK INGREDIENT - ANIMAL DRUG
Date: 20260119

ACTIVE INGREDIENTS: SULFADIMETHOXINE 1 g/1 g

Sulfadimethoxine